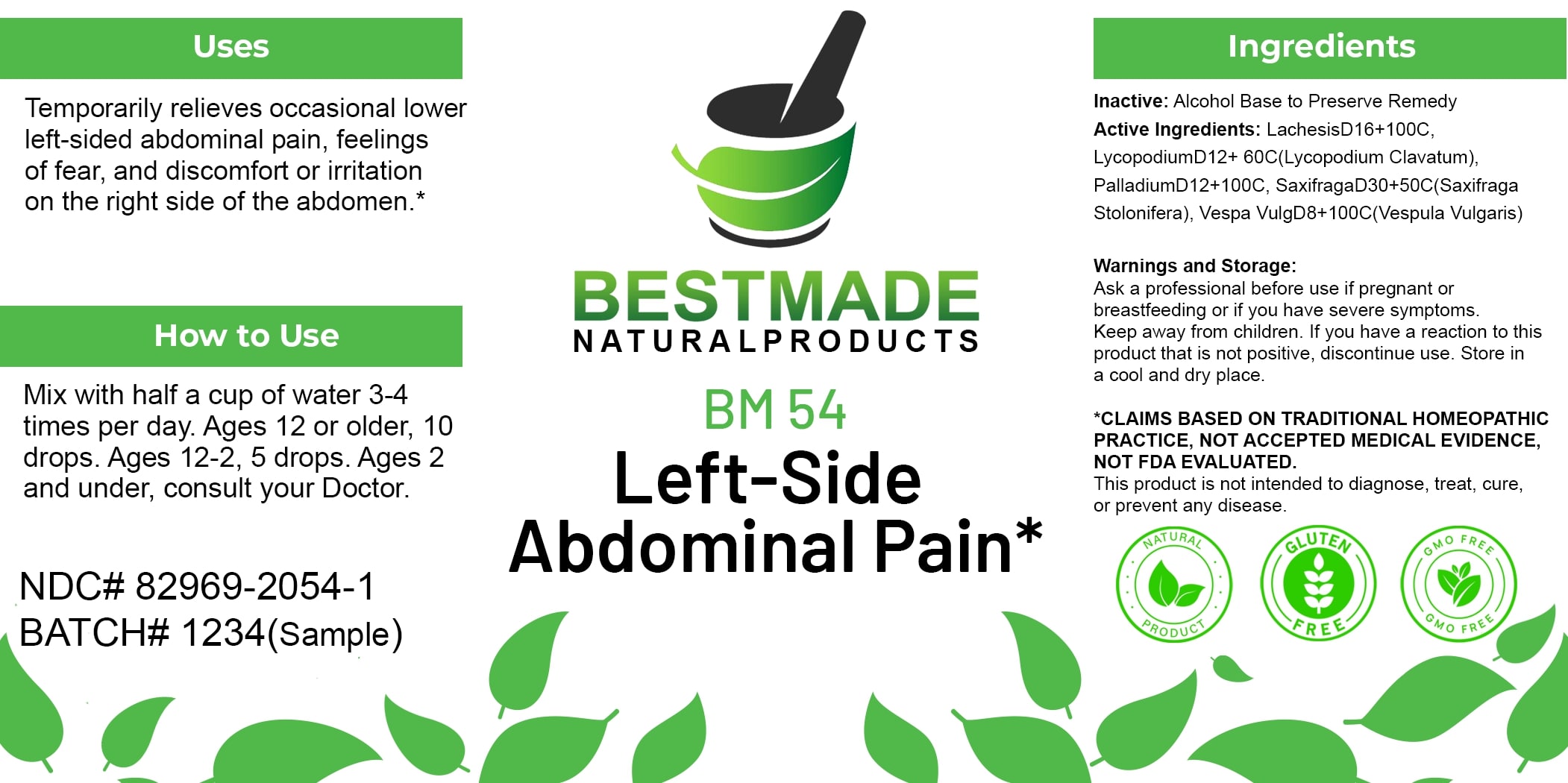 DRUG LABEL: Bestmade Natural Products BM54
NDC: 82969-2054 | Form: LIQUID
Manufacturer: Bestmade Natural Products
Category: homeopathic | Type: HUMAN OTC DRUG LABEL
Date: 20250124

ACTIVE INGREDIENTS: LYCOPODIUM CLAVATUM SPORE 60 [hp_C]/100 [hp_C]; SAXIFRAGA STOLONIFERA WHOLE 50 [hp_C]/100 [hp_C]; PALLADIUM 100 [hp_C]/100 [hp_C]; VESPULA VULGARIS WHOLE 100 [hp_C]/100 [hp_C]; LACHESIS MUTA VENOM 100 [hp_C]/100 [hp_C]
INACTIVE INGREDIENTS: ALCOHOL 100 [hp_C]/100 [hp_C]

BM54

DOSAGE AND ADMINISTRATION

How to Use

Mix with half a cup of water 3-4 times per day. Ages 12 or older, 10 drops. Ages 12-2, 5 drops. Ages 2 and under, consult your Doctor.

INACTIVE INGREDIENT

Ingredients

Inactive: Alcohol Base to Preserve Remedy

ACTIVE INGREDIENT

Active Ingredients: Lachesis D16+100C, Lycopodium D12+60C (Lycopodium Clavatum), Palladium D12+100C, Saxifraga D30+50C (Saxifraga Stolonifera), Vespa Vulg D8+100C (Vespula Vulgaris)

Uses

Temporarily relieves occasional lower left-sided abdominal pain, feelings of fear, and discomfort or irritation on the right side of the abdomen.*

*CLAIMS BASED ON TRADITIONAL HOMEOPATHIC PRACTICE, NOT ACCEPTED MEDICAL EVIDENCE. NOT FDA EVALUATED.

This product is not intended to diagnose, treat, cure, or prevent any disease.

Uses

Temporarily relieves occasional lower left-sided abdominal pain, feelings of fear, and discomfort or irritation on the right side of the abdomen.*

*CLAIMS BASED ON TRADITIONAL HOMEOPATHIC PRACTICE, NOT ACCEPTED MEDICAL EVIDENCE. NOT FDA EVALUATED.

This product is not intended to diagnose, treat, cure, or prevent any disease.

KEEP OUT OF REACH OF CHILDREN

Warnings and Storage:

Ask a professional before use if pregnant or breastfeeding or if you have severe symptoms. Keep away from children. If you have a reaction to this product that is not positive, discontinue use. Store in a cool and dry place.

Warnings and Storage:

Ask a professional before use if pregnant or breastfeeding or if you have severe symptoms. Keep away from children. If you have a reaction to this product that is not positive, discontinue use. Store in a cool and dry place.

*CLAIMS BASED ON TRADITIONAL HOMEOPATHIC PRACTICE, NOT ACCEPTED MEDICAL EVIDENCE. NOT FDA EVALUATED.

This product is not intended to diagnose, treat, cure, or prevent any disease.

Entire package label